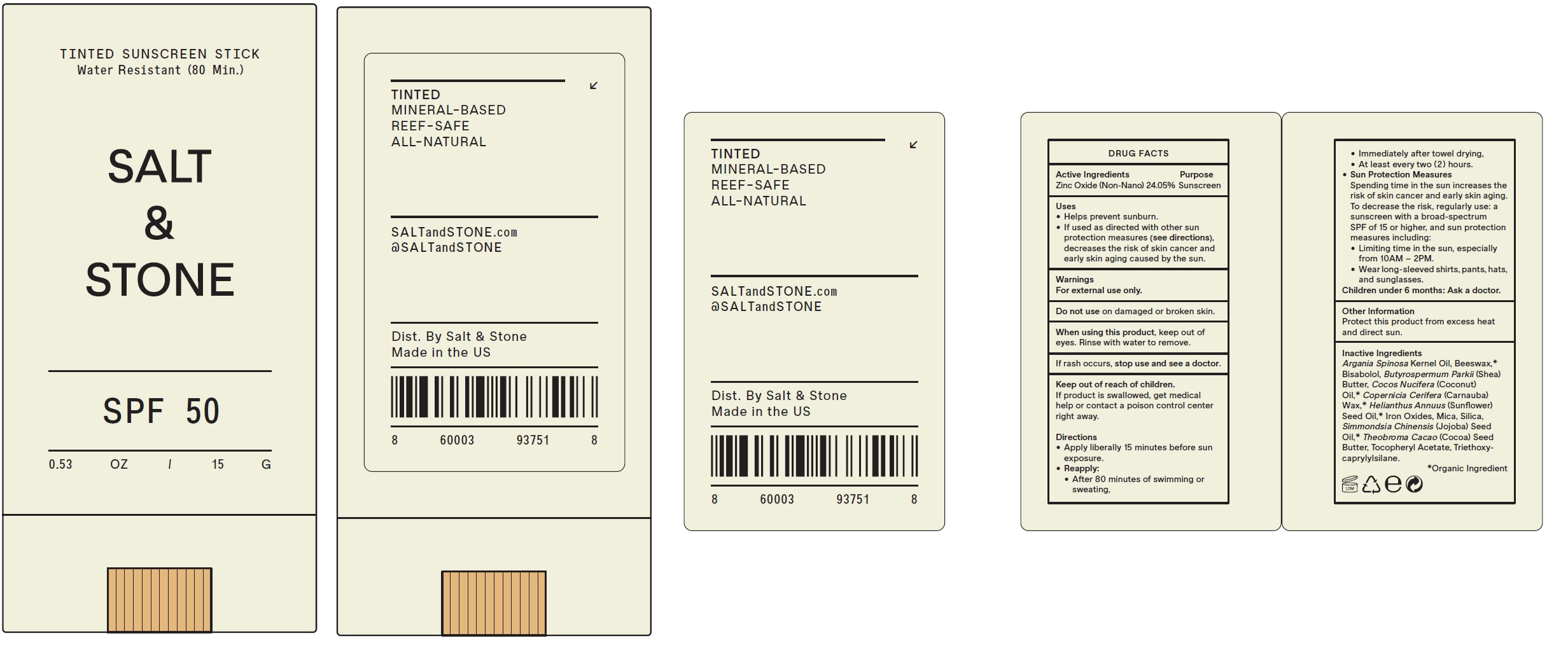 DRUG LABEL: Salt and Stone Tinted Sunscreen  SPF 50
NDC: 71585-138 | Form: STICK
Manufacturer: Salt and Stone LLC
Category: otc | Type: HUMAN OTC DRUG LABEL
Date: 20231028

ACTIVE INGREDIENTS: ZINC OXIDE 0.2405 g/1 g
INACTIVE INGREDIENTS: ARGAN OIL; YELLOW WAX; LEVOMENOL; SHEA BUTTER; COCONUT OIL; CARNAUBA WAX; SUNFLOWER OIL; FERRIC OXIDE RED; MICA; SILICON DIOXIDE; JOJOBA OIL; COCOA BUTTER; .ALPHA.-TOCOPHEROL ACETATE; TRIETHOXYCAPRYLYLSILANE

Salt & Stone Tinted Sunscreen Stick SPF 50, 0.53 Oz.(15 g)

Active Ingredients

Zinc Oxide (Non-Nano) 24. 05%

Purpose

Sunscreen

Uses

• Helps prevent sunburn. • If used as directed with other sun protection measures (see directions), decreases the risk of skin cancer and early skin aging caused by the sun.

Warnings

For external use only.

on damaged or broken skin. Do not use

WHEN USING

keep out of eyes. Rinse with water to remove. When using this product,

STOP USE

If rash occurs, stop use and see a doctor.

Keep out of reach of children.

If product is swallowed, get medical help or contact a poison control center right away.

Directions

- Apply liberally 15 minutes before sun exposure.
- • After 80 minutes of swimming or sweating, • Immediately after towel drying, • At least every two (2) hours. Reapply:
- Spending time in the sun increases the risk of skin cancer and early skin aging. To decrease the risk, regularly use: a sunscreen with a broad-spectrum SPF of 15 or higher, and sun protection measures including: • Limiting time in the sun, especially from 10AM – 2PM. • Wear long-sleeved shirts, pants, hats, and sunglasses. Sun Protection Measures
- Children under 6 months: Ask a doctor.

Other Information

Protect this product from excess heat and direct sun.

Inactive Ingredients

Argania Spinosa Kernel Oil, Beeswax,* Bisabolol, Butyrospermum Parkii (Shea) Butter, Cocos Nucifera (Coconut) Oil,* Copernicia Cerifera (Carnauba) Wax,* Helianthus Annuus (Sunflower) Seed Oil,* Iron Oxides, Mica, Silica, Simmondsia Chinensis (Jojoba) Seed Oil,* Theobroma Cacao (Cocoa) Seed Butter, Tocopheryl Acetate, Triethoxycaprylylsilane.